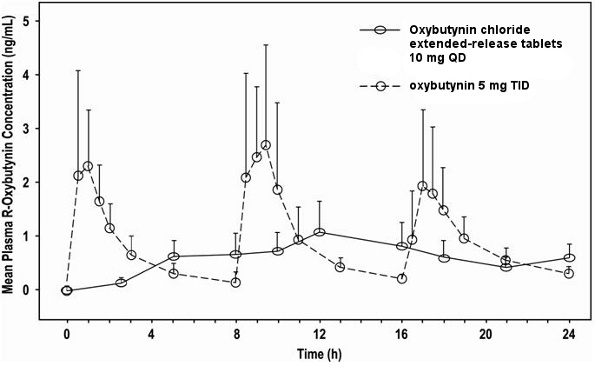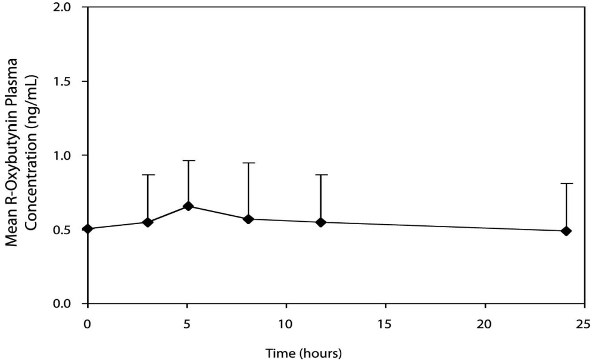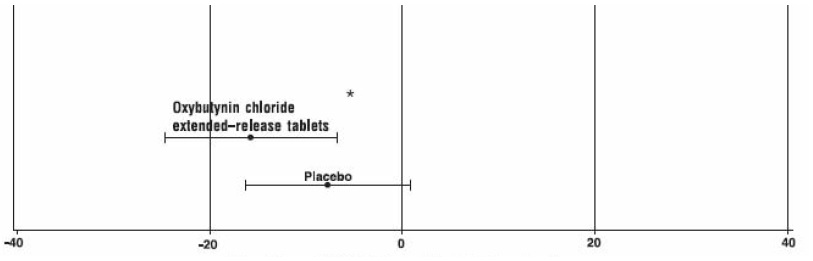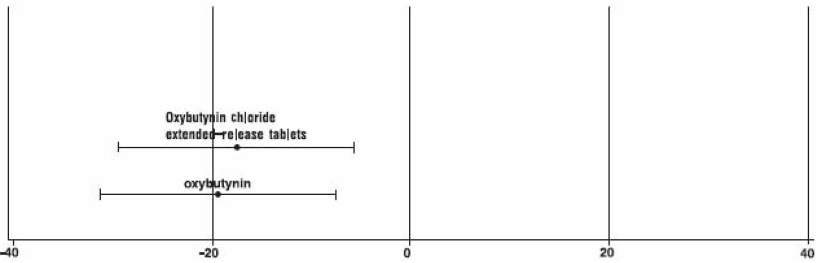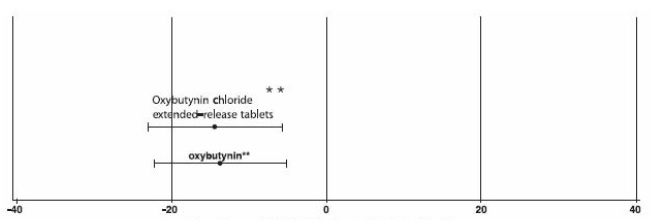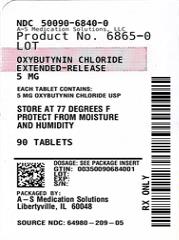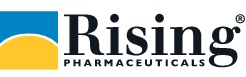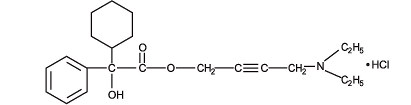 DRUG LABEL: Oxybutynin Chloride
NDC: 50090-6840 | Form: TABLET, EXTENDED RELEASE
Manufacturer: A-S Medication Solutions
Category: prescription | Type: Human Prescription Drug Label
Date: 20260217

ACTIVE INGREDIENTS: OXYBUTYNIN CHLORIDE 5 mg/1 1
INACTIVE INGREDIENTS: PEG-160M; PEG-5M; HYPROMELLOSE 2910 (3 MPA.S); SODIUM CHLORIDE; BHT; FERRIC OXIDE YELLOW; FERROSOFERRIC OXIDE; SILICA; MAGNESIUM STEARATE; CELLULOSE ACETATE; POLYETHYLENE GLYCOL 3350; TITANIUM DIOXIDE; LACTOSE MONOHYDRATE; TRIACETIN; SHELLAC; HYPROMELLOSE 2910 (6 MPA.S); PROPYLENE GLYCOL

HIGHLIGHTS OF PRESCRIBING INFORMATION

These highlights do not include all the information needed to use OXYBUTYNIN CHLORIDE EXTENDED-RELEASE TABLETS safely and effectively. See full prescribing information for OXYBUTYNIN CHLORIDE EXTENDED-RELEASE TABLETS.
OXYBUTYNIN CHLORIDE Extended-Release Tablets, for oral use
Initial U.S. Approval: 1975

1 INDICATIONS AND USAGE

- Oxybutynin chloride extended-release tablets are a muscarinic antagonist indicated for the treatment of overactive bladder with symptoms of urge urinary incontinence, urgency, and frequency. (1)
- Oxybutynin chloride extended-release tablets are also indicated for the treatment of pediatric patients aged 6 years and older with symptoms of detrusor overactivity associated with a neurological condition (e.g., spina bifida). (1)

2 DOSAGE AND ADMINISTRATION

Oxybutynin chloride extended-release tablets must be swallowed whole with the aid of liquids, and must not be chewed, divided, or crushed. Oxybutynin chloride extended-release tablets may be administered with or without food. (2)

- Adults: Start with 5 mg or 10 mg, once daily at approximately the same time every day. Dose should not exceed 30 mg per day. (2.1)
- Pediatric patients (6 years of age or older): Start with 5 mg, once daily at approximately the same time every day. Dose should not exceed 20 mg per day. (2.2)

3 DOSAGE FORMS AND STRENGTHS

Extended release tablets 5 mg, 10 mg and 15 mg (3)

4 CONTRAINDICATIONS

- Urinary retention (4)
- Gastric Retention (4)
- Uncontrolled narrow angle glaucoma (4)
- Known hypersensitivity to oxybutynin chloride extended-release tablets, oxybutynin or any component of oxybutynin chloride extended-release tablets. (4)

5 WARNINGS AND PRECAUTIONS

- Angioedema: Angioedema has been reported with oxybutynin. If symptoms of angioedema occur, discontinue oxybutynin chloride extended-release tablets immediately and initiate appropriate therapy. (5.1)
- Central Nervous System (CNS) effects: CNS effects have been reported with oxybutynin. If patient experiences anticholinergic CNS effects, consider dose adjustment or discontinuation of oxybutynin chloride extended-release tablets. (5.2)
- Use with caution due to aggravation of symptoms:
  - Pre-existing dementia in patients treated with cholinesterase inhibitors (5.2),
  - Parkinson’s disease (5.2),
  - Myasthenia gravis (5.3), and
  - Decreased gastrointestinal motility in patients with autonomic neuropathy (5.4).
- Urinary Retention: Use with caution in patients with clinically significant bladder outflow obstruction because of the risk of urinary retention. (5.5)
- Gastrointestinal Adverse Reactions: Use with caution in patients with gastrointestinal obstructive disorders or decreased intestinal motility due to risk of gastric retention. Use with caution in patients with gastroesophageal reflux or in patients concurrently taking drugs that can exacerbate esophagitis. (5.6)

6 ADVERSE REACTIONS

The most common (incidence ≥ 5%) adverse reactions were dry mouth, constipation, diarrhea, headache, somnolence, and dizziness. (6)
To report SUSPECTED ADVERSE REACTIONS, contact Rising Pharma Holdings, Inc. at 1-844-874-7464 or FDA at 1-800-FDA-1088 or www.fda.gov/medwatch.

7 DRUG INTERACTIONS

- Co-administration with other anticholinergic drugs may increase the frequency and/or severity of anticholinergic-like effects. (7)
- Co-administration with strong cytochrome P450 (CYP) 3A4 inhibitors (e.g., ketoconazole) increases the systemic exposure of oxybutynin. (7)

8 USE IN SPECIFIC POPULATIONS

- Pediatric Use: Oxybutynin chloride extended-release tablets are not recommended in pediatric patients who cannot swallow the tablet whole without chewing, dividing or crushing, or in children under the age of 6 years. (8.4)
- Renal or Hepatic Impairment: There have been no studies conducted in patients with renal or hepatic impairment. (8.6, 8.7)

FULL PRESCRIBING INFORMATION

1 INDICATIONS AND USAGE

Oxybutynin chloride extended-release tablets are a muscarinic antagonist indicated for the treatment of overactive bladder with symptoms of urge urinary incontinence, urgency, and frequency.
Oxybutynin chloride extended-release tablets are also indicated for the treatment of pediatric patients aged 6 years and older with symptoms of detrusor overactivity associated with a neurological condition (e.g., spina bifida).

2 DOSAGE AND ADMINISTRATION

Oxybutynin chloride extended-release tablets must be swallowed whole with the aid of liquids, and must not be chewed, divided, or crushed.
Oxybutynin chloride extended-release tablets may be administered with or without food.

2.1 Adults

The recommended starting dose of oxybutynin chloride extended-release tablets are 5 or 10 mg once daily at approximately the same time each day. Dosage may be adjusted in 5-mg increments to achieve a balance of efficacy and tolerability (up to a maximum of 30 mg/day). In general, dosage adjustment may proceed at approximately weekly intervals.

2.2 Pediatric Patients Aged 6 Years of Age and Older

The recommended starting dose of oxybutynin chloride extended-release tablets is 5 mg once daily at approximately the same time each day. Dosage may be adjusted in 5-mg increments to achieve a balance of efficacy and tolerability (up to a maximum of 20 mg/day).

3 DOSAGE FORMS AND STRENGTHS

Oxybutynin chloride extended-release tablets USP are available as 5, 10 and 15 mg tablets for oral use:
5 mg: Pale yellow colored, round, biconvex tablets with orifice and "P 5" imprinted with black ink.
10 mg: Pink colored, round, biconvex tablets with orifice and "P 10" imprinted with black ink.
15 mg: Grey colored, round, biconvex tablets with orifice and "P 15" imprinted with black ink.

4 CONTRAINDICATIONS

Oxybutynin chloride extended-release tablets are contraindicated in patients with urinary retention, gastric retention and other severe decreased gastrointestinal motility conditions, uncontrolled narrow-angle glaucoma.
Oxybutynin chloride extended-release tablets are also contraindicated in patients who have demonstrated hypersensitivity to the drug substance or other components of the product. There have been reports of hypersensitivity reactions, including anaphylaxis and angioedema.

5 WARNINGS AND PRECAUTIONS

5.1 Angioedema

Angioedema of the face, lips, tongue and/or larynx has been reported with oxybutynin. In some cases, angioedema occurred after the first dose. Angioedema associated with upper airway swelling may be life-threatening. If involvement of the tongue, hypopharynx, or larynx occurs, oxybutynin should be promptly discontinued and appropriate therapy and/or measures necessary to ensure a patent airway should be promptly provided.

5.2 Central Nervous System Effects

Oxybutynin is associated with anticholinergic central nervous system (CNS) effects [see Adverse Reactions (6)]. A variety of CNS anticholinergic effects have been reported, including hallucinations, agitation, confusion and somnolence. Patients should be monitored for signs of anticholinergic CNS effects, particularly in the first few months after beginning treatment or increasing the dose. Advise patients not to drive or operate heavy machinery until they know how oxybutynin chloride extended-release tablets affects them. If a patient experiences anticholinergic CNS effects, dose reduction or drug discontinuation should be considered.
Oxybutynin chloride extended-release tablets should be used with caution in patients with preexisting dementia treated with cholinesterase inhibitors due to the risk of aggravation of symptoms.
Oxybutynin chloride extended-release tablets should be used with caution in patients with Parkinson’s disease due to the risk of aggravation of symptoms.

5.3 Worsening of Symptoms of Myasthenia Gravis

Oxybutynin chloride extended-release tablets should be used with caution in patients with myasthenia gravis due to the risk of aggravation of symptoms.

5.4 Worsening of Symptoms of Decreased Gastrointestinal Motility in Patients with Autonomic Neuropathy

Oxybutynin chloride extended-release tablets should be used with caution in patients with autonomic neuropathy due to the risk of aggravation of symptoms of decreased gastrointestinal motility.

5.5 Urinary Retention

Oxybutynin chloride extended-release tablets should be administered with caution to patients with clinically significant bladder outflow obstruction because of the risk of urinary retention [see Contraindications (4)].

5.6 Gastrointestinal Adverse Reactions

Oxybutynin chloride extended-release tablets should be administered with caution to patients with gastrointestinal obstructive disorders because of the risk of gastric retention [see Contraindications (4)].
Oxybutynin chloride extended-release tablets, like other anticholinergic drugs, may decrease gastrointestinal motility and should be used with caution in patients with conditions such as ulcerative colitis and intestinal atony.
Oxybutynin chloride extended-release tablets should be used with caution in patients who have gastroesophageal reflux and/or who are concurrently taking drugs (such as bisphosphonates) that can cause or exacerbate esophagitis.
As with any other nondeformable material, caution should be used when administering Oxybutynin chloride extended-release tablets to patients with preexisting severe gastrointestinal narrowing (pathologic or iatrogenic). There have been rare reports of obstructive symptoms in patients with known strictures in association with the ingestion of other drugs in nondeformable controlled-release formulations.

6 ADVERSE REACTIONS

6.1 Clinical Trials Experience

Because clinical trials are conducted under widely varying conditions, the adverse reaction rates observed in the clinical trials of a drug cannot be directly compared to rates in the clinical trials of another drug and may not reflect the rates observed in clinical practice.

The safety and efficacy of oxybutynin chloride extended-release tablets (5 to 30 mg/day) was evaluated in 774 adult subjects who participated in five double-blind, controlled clinical trials. In four of the five studies, oxybutynin chloride immediate release tablets (5 to 20 mg/day in 199 subjects) was an active comparator. Adverse reactions reported by ≥ 1% of subjects are shown in Table 1.

Table 1: Adverse Drug Reactions Reported by ≥ 1% of Oxybutynin Chloride Extended-Release Tablets-treated Adult Subjects in Five Double-blind, Controlled Clinical Trials of Oxybutynin Chloride Extended-Release Tablets.
System/Organ Class Preferred Term | Oxybutynin Chloride Extended-Release Tablets 5 to 30 mg/day n = 774 % | Oxybutynin Chloride IR^1 Tablets 5 to 20 mg/day n = 199 %
Psychiatric Disorders
Insomnia | 3.0 | 5.5
Nervous System Disorders
Headache | 7.5 | 8.0
Somnolence | 5.6 | 14.1
Dizziness | 5.0 | 16.6
Dysgeusia | 1.6 | 1.5
Eye Disorders
Vision blurred | 4.3 | 9.6
Dry eye | 3.1 | 2.5
Respiratory, Thoracic and Mediastinal Disorders
Cough | 1.9 | 3.0
Oropharyngeal pain | 1.9 | 1.5
Dry throat | 1.7 | 2.5
Nasal dryness | 1.7 | 4.5
Gastrointestinal Disorders
Dry mouth | 34.9 | 72.4
Constipation | 8.7 | 15.1
Diarrhea | 7.9 | 6.5
Dyspepsia | 4.5 | 6.0
Nausea | 4.5 | 11.6
Abdominal pain | 1.6 | 2.0
Vomiting | 1.3 | 1.5
Flatulence | 1.2 | 2.5
Gastro-esophageal reflux disease | 1.0 | 0.5
Skin and Subcutaneous Tissue Disorders
Dry skin | 1.8 | 2.5
Pruritus | 1.3 | 1.5
Renal and Urinary Disorders
Dysuria | 1.9 | 2.0
Urinary hesitation | 1.9 | 8.5
Urinary retention | 1.2 | 3.0
General Disorders and Administration Site Conditions
Fatigue | 2.6 | 3.0
Investigations
Residual urine volume ^2 | 2.3 | 3.5
^1IR=immediate release
^2The bundled term residual urine volume consists of the preferred terms residual urine volume and residual urine volume increased.

The discontinuation rate due to adverse reactions was 4.4% with oxybutynin chloride extended-release tablets compared to 0% with oxybutynin chloride immediate release tablets. The most frequent adverse reaction causing discontinuation of study medication was dry mouth (0.7%).
The following adverse reactions were reported by < 1% of oxybutynin chloride extended-release tablets-treated patients and at a higher incidence than placebo in clinical trials: Metabolism and Nutrition Disorders: anorexia, fluid retention; Vascular disorders: hot flush; Respiratory, thoracic and mediastinal disorders: dysphonia; Gastrointestinal Disorders: dysphagia, frequent bowel movements; General disorders and administration site conditions: chest discomfort, thirst.

6.2 Postmarketing Experience

The following additional adverse reactions have been reported from worldwide postmarketing experience with oxybutynin chloride extended-release tablets. Because postmarketing reactions are reported voluntarily from a population of uncertain size, it is not always possible to reliably estimate their frequency or establish a causal relationship to drug exposure.

Infections and Infestations: Urinary tract infection; Psychiatric Disorders: psychotic disorder, agitation, confusional state, hallucinations, memory impairment, abnormal behavior; Nervous System Disorders: convulsions; Eye Disorders: glaucoma; Respiratory, Thoracic and Mediastinal Disorders: nasal congestion; Cardiac Disorders: arrhythmia, tachycardia, palpitations, QT interval prolongation; Vascular Disorders: flushing, hypertension; Skin and Subcutaneous Tissue Disorders: rash; Renal and Urinary Disorders: impotence; General Disorders and Administration Site Conditions: hypersensitivity reactions, including angioedema with airway obstruction, urticaria, and face edema; anaphylactic reactions requiring hospitalization for emergency treatment; Injury, poisoning and procedural complications: fall.
Additional adverse events reported with some other oxybutynin chloride formulations include: cycloplegia, mydriasis, and suppression of lactation. In one reported case, concomitant use of oxybutynin with carbamazepine and dantrolene was associated with adverse events of vomiting, drowsiness, confusion, unsteadiness, slurred speech and nystagmus, suggestive of carbamazepine toxicity.

7 DRUG INTERACTIONS

The concomitant use of oxybutynin with other anticholinergic drugs or with other agents which produce dry mouth, constipation, somnolence (drowsiness), and/or other anticholinergic-like effects may increase the frequency and/or severity of such effects.

Anticholinergic agents may potentially alter the absorption of some concomitantly administered drugs due to anticholinergic effects on gastrointestinal motility. This may be of concern for drugs with a narrow therapeutic index. Anticholinergic agents may also antagonize the effects of prokinetic agents, such as metoclopramide.

Mean oxybutynin plasma concentrations were approximately 2 fold higher when oxybutynin chloride extended-release tablets were administered with ketoconazole, a potent CYP3A4 inhibitor. Other inhibitors of the cytochrome P450 3A4 enzyme system, such as antimycotic agents (e.g., itraconazole and miconazole) or macrolide antibiotics (e.g., erythromycin and clarithromycin), may alter oxybutynin mean pharmacokinetic parameters (i.e., Cmax and AUC). The clinical relevance of such potential interactions is not known. Caution should be used when such drugs are co-administered.

8 USE IN SPECIFIC POPULATIONS

8.1 Pregnancy

Risk Summary
There are no adequate data on oxybutynin chloride extended-release tablets use in pregnant women to evaluate for a drug-associated risk of major birth defects, miscarriage or adverse maternal or fetal outcomes.

In the U.S. general population, the estimated background risk of major birth defects and miscarriage in clinically recognized pregnancies is 2-4% and 15-20%, respectively. The background risk of major birth defects and miscarriage for the indicated population is unknown.

8.2 Lactation

Risk Summary
There are no data on the presence of oxybutynin in human milk, the effects on the breastfed infant, or the effects of oxybutynin chloride extended-release tablets on milk production. The developmental and health benefits of breastfeeding should be considered along with the mother’s clinical need for oxybutynin chloride extended-release tablets and any potential adverse effects on the breastfed child from oxybutynin chloride extended-release tablets or from the underlying maternal condition.

8.4 Pediatric Use

The safety and efficacy of oxybutynin chloride extended-release tablets were studied in 60 children in a 24-week, open-label, non-randomized trial. Patients were aged 6-15 years, all had symptoms of detrusor overactivity in association with a neurological condition (e.g., spina bifida), all used clean intermittent catheterization, and all were current users of oxybutynin chloride. Study results demonstrated that administration of oxybutynin chloride extended-release tablets 5 to 20 mg/day was associated with an increase from baseline in mean urine volume per catheterization from 108 mL to 136 mL, an increase from baseline in mean urine volume after morning awakening from 148 mL to 189 mL, and an increase from baseline in the mean percentage of catheterizations without a leaking episode from 34% to 51%.
Urodynamic results were consistent with clinical results. Administration of oxybutynin chloride extended-release tablets resulted in an increase from baseline in mean maximum cystometric capacity from 185 mL to 254 mL, a decrease from baseline in mean detrusor pressure at maximum cystometric capacity from 44 cm H2O to 33 cm H2O, and a reduction in the percentage of patients demonstrating uninhibited detrusor contractions (of at least 15 cm H2O) from 60% to 28%.

The pharmacokinetics of oxybutynin chloride extended-release tablets in these patients were consistent with those reported for adults [see Clinical Pharmacology (12.3)].
Oxybutynin chloride extended-release tablets are not recommended in pediatric patients who cannot swallow the tablet whole without chewing, dividing, or crushing, or in children under the age of 6.

8.5 Geriatric Use

The rate and severity of anticholinergic effects reported by patients less than 65 years old and those 65 years and older were similar. The pharmacokinetics of oxybutynin chloride extended-release tablets were similar in all patients studied (up to 78 years of age).

8.6 Renal Impairment

There were no studies conducted with oxybutynin chloride extended-release tablets in patients with renal impairment.

8.7 Hepatic Impairment

There were no studies conducted with oxybutynin chloride extended-release tablets in patients with hepatic impairment.

10 OVERDOSAGE

The continuous release of oxybutynin from oxybutynin chloride extended-release tablets should be considered in the treatment of overdosage. Patients should be monitored for at least 24 hours. Treatment should be symptomatic and supportive. A cathartic may be administered.
Overdosage with oxybutynin chloride has been associated with anticholinergic effects including central nervous system excitation, flushing, fever, dehydration, cardiac arrhythmia, vomiting, and urinary retention.
Ingestion of 100 mg oxybutynin chloride in association with alcohol has been reported in a 13-year-old boy who experienced memory loss, and a 34-year-old woman who developed stupor, followed by disorientation and agitation on awakening, dilated pupils, dry skin, cardiac arrhythmia, and retention of urine. Both patients fully recovered with symptomatic treatment.

11 DESCRIPTION

Oxybutynin chloride USP is an antispasmodic, muscarinic antagonist. Each oxybutynin chloride extended-release tablet USP contains 5 mg, 10 mg or 15 mg of oxybutynin chloride USP, formulated as a once-a-day controlled-release tablet for oral administration. Oxybutynin chloride is administered as a racemate of R- and S-enantiomers.
Chemically, oxybutynin chloride is d,l (racemic) 4-diethylamino-2-butynylphenylcyclohexylglycolate hydrochloride. The empirical formula of oxybutynin chloride is C22H31NO3•HCl.
Its structural formula is:

Oxybutynin chloride USP is a white crystalline solid with a molecular weight of 393.9. It is readily soluble in water and acids, but relatively insoluble in alkalis.
Oxybutynin chloride extended-release tablet, USP also contains the following inert ingredients: polyethylene oxide, hypromellose, sodium chloride, butylated hydroxytoluene, ferric oxide (yellow), ferric oxide (red), ferric oxide (black), colloidal silicon dioxide, magnesium stearate, cellulose acetate, polyethylene glycol, titanium dioxide, lactose monohydrate, triacetin, shellac, and propylene glycol.

System Components and Performance
Oxybutynin chloride extended-release tablets USP uses osmotic pressure to deliver oxybutynin chloride at a controlled rate over approximately 24 hours. The system, which resembles a conventional tablet in appearance, comprises an osmotically active bilayer core surrounded by a semipermeable membrane. The bilayer core is composed of a drug layer containing the drug and excipients, and a push layer containing osmotically active components. There is a precision-laser drilled orifice in the semipermeable membrane on the drug-layer side of the tablet. In an aqueous environment, such as the gastrointestinal tract, water permeates through the membrane into the tablet core, causing the drug to go into suspension and the push layer to expand. This expansion pushes the suspended drug out through the orifice. The semipermeable membrane controls the rate at which water permeates into the tablet core, which in turn controls the rate of drug delivery. The controlled rate of drug delivery into the gastrointestinal lumen is thus independent of pH or gastrointestinal motility. The function of oxybutynin chloride extended-release tablets depends on the existence of an osmotic gradient between the contents of the bilayer core and the fluid in the gastrointestinal tract. Since the osmotic gradient remains constant, drug delivery remains essentially constant. The biologically inert components of the tablet remain intact during gastrointestinal transit and are eliminated in the feces as an insoluble shell.
Product meets USP Dissolution Test 6

12 CLINICAL PHARMACOLOGY

12.1 Mechanism of Action

Oxybutynin relaxes bladder smooth muscle. Oxybutynin chloride exerts a direct antispasmodic effect on smooth muscle and inhibits the muscarinic action of acetylcholine on smooth muscle. No blocking effects occur at skeletal neuromuscular junctions or autonomic ganglia (antinicotinic effects).
Antimuscarinic activity resides predominantly in the R-isomer. A metabolite, desethyloxybutynin, has pharmacological activity similar to that of oxybutynin in in vitro studies.

12.2 Pharmacodynamics

In patients with conditions characterized by involuntary bladder contractions, cystometric studies have demonstrated that oxybutynin increases bladder (vesical) capacity, diminishes the frequency of uninhibited contractions of the detrusor muscle, and delays the initial desire to void.

12.3 Pharmacokinetics

Absorption
Following the first dose of oxybutynin chloride extended-release tablets, oxybutynin plasma concentrations rise for 4 to 6 hours; thereafter steady concentrations are maintained for up to 24 hours, minimizing fluctuations between peak and trough concentrations associated with oxybutynin.
The relative bioavailabilities of R- and S-oxybutynin from oxybutynin chloride extended-release tablets are 156% and 187%, respectively, compared with oxybutynin. The mean pharmacokinetic parameters for R- and S-oxybutynin are summarized in Table 2. The plasma concentration-time profiles for R- and S-oxybutynin are similar in shape; Figure 1 shows the profile for R-oxybutynin.

Table 2: Mean (SD) R- and S-Oxybutynin Pharmacokinetic Parameters Following a Single Dose of Oxybutynin Chloride Extended-Release Tablets 10 mg (n=43)

Parameters (units) | R-Oxybutynin | S-Oxybutynin
Cmax (ng/mL) | 1.0 (0.6) | 1.8 (1.0)
Tmax (h) | 12.7 (5.4) | 11.8 (5.3)
t1/2 (h) | 13.2 (6.2) | 12.4 (6.1)
AUC(0-48) (ng•h/mL) | 18.4 (10.3) | 34.2 (16.9)
AUCinf (ng•h/mL) | 21.3 (12.2) | 39.5 (21.2)

Figure 1: Mean R-oxybutynin plasma concentrations following a single dose of Oxybutynin Chloride Extended-Release Tablets 10 mg and oxybutynin 5 mg administered every 8 hours (n=23 for each treatment)

Steady state oxybutynin plasma concentrations are achieved by Day 3 of repeated oxybutynin chloride extended-release tablets dosing, with no observed drug accumulation or change in oxybutynin and desethyloxybutynin pharmacokinetic parameters.

Oxybutynin chloride extended-release tablets steady state pharmacokinetics were studied in 19 children aged 5-15 years with detrusor overactivity associated with a neurological condition (e.g., spina bifida). The children were on oxybutynin chloride extended-release tablets total daily dose ranging from 5 to 20 mg (0.10 to 0.77 mg/kg). Sparse sampling technique was used to obtain serum samples. When all available data are normalized to an equivalent of 5 mg per day of oxybutynin chloride extended-release tablets, the mean pharmacokinetic parameters derived for R- and S-oxybutynin and R- and S-desethyloxybutynin are summarized in Table 3. The plasma-time concentration profiles for R- and S-oxybutynin are similar in shape; Figure 2 shows the profile for R-oxybutynin when all available data are normalized to an equivalent of 5 mg per day.

Table 3: Mean ±SD R- and S-Oxybutynin and R- and S-Desethyloxybutynin Pharmacokinetic Parameters in Children Aged 5-15 Following Administration of 5 to 20 mg Oxybutynin Chloride Extended-Release Tablets Once Daily (n=19), All Available Data Normalized to an Equivalent of Oxybutynin Chloride Extended-Release Tablets 5 mg Once Daily

 | R-Oxybutynin | S-Oxybutynin | R-Desethyloxybutynin | S-Desethyloxybutynin
Cmax (ng/mL) Tmax (h) AUC (ng•h/mL) | 0.7 ± 0.4 5.0 12.8 ± 7.0 | 1.3 ± 0.8 5.0 23.7 ± 14.4 | 7.8 ± 3.7 5.0 125.1 ± 66.7 | 4.2 ± 2.3 5.0 73.6 ± 47.7

Figure 2: Mean steady state (±SD) R-oxybutynin plasma concentrations following administration of 5 to 20 mg Oxybutynin Chloride Extended-Release Tablets once daily in children aged 5-15. Plot represents all available data normalized to an equivalent of Oxybutynin Chloride Extended-Release Tablet 5 mg once daily.

Food Effects

The rate and extent of absorption and metabolism of oxybutynin are similar under fed and fasted conditions.

Distribution
Oxybutynin is widely distributed in body tissues following systemic absorption. The volume of distribution is 193 L after intravenous administration of 5 mg oxybutynin chloride. Both enantiomers of oxybutynin are highly bound (> 99%) to plasma proteins. Both enantiomers of N-desethyloxybutynin are also highly bound (> 97%) to plasma proteins. The major binding protein is alpha-1 acid glycoprotein.

Metabolism
Oxybutynin is metabolized primarily by the cytochrome P450 enzyme systems, particularly CYP3A4 found mostly in the liver and gut wall. Its metabolic products include phenylcyclohexylglycolic acid, which is pharmacologically inactive, and desethyloxybutynin, which is pharmacologically active. Following oxybutynin chloride extended-release tablets administration, plasma concentrations of R-and S-desethyloxybutynin are 73% and 92%, respectively, of concentrations observed with oxybutynin.

Excretion
Oxybutynin is extensively metabolized by the liver, with less than 0.1% of the administered dose excreted unchanged in the urine. Also, less than 0.1% of the administered dose is excreted as the metabolite desethyloxybutynin.

Dose Proportionality
Pharmacokinetic parameters of oxybutynin and desethyloxybutynin (Cmax and AUC) following administration of 5-20 mg of oxybutynin chloride extended-release tablets are dose proportional.

Use in Specific Populations

Pediatric
The pharmacokinetics of oxybutynin chloride extended release tablets were evaluated in 19 children aged 5-15 years with detrusor overactivity associated with a neurological condition (e.g., spina bifida). The pharmacokinetics of oxybutynin chloride extended-release tablets in these pediatric patients were consistent with those reported for adults (see Tables 2 and 3, and Figures 1 and 2 above).
GenderThere are no significant differences in the pharmacokinetics of oxybutynin in healthy male and female volunteers following administration of oxybutynin chloride extended-release tablets.
Race
Available data suggest that there are no significant differences in the pharmacokinetics of oxybutynin based on race in healthy volunteers following administration of oxybutynin chloride extended-release tablets.

13 NONCLINICAL TOXICOLOGY

13.1 Carcinogenesis, Mutagenesis, Impairment of Fertility

Carcinogenesis
A 24-month study in rats at dosages of oxybutynin chloride of 20, 80, and 160 mg/kg/day showed no evidence of carcinogenicity. These doses are approximately 6, 25, and 50 times the maximum human exposure, based on a human equivalent dose taking into account normalization of body surface area.

Mutagenesis
Oxybutynin chloride showed no increase of mutagenic activity when tested in Schizosaccharomyces pompholiciformis, Saccharomyces cerevisiae, and Salmonella typhimurium test systems.

Impairment of Fertility
No impairment of fertility was seen in rats at dosages up to 75 mg/kg/day (24 times the MRHD on a mg/m^2 basis) when administered for 2 weeks prior to mating in females and for 9 weeks prior to mating in males.

14 CLINICAL STUDIES

Oxybutynin chloride extended-release tablets were evaluated for the treatment of patients with overactive bladder with symptoms of urge urinary incontinence, urgency, and frequency in three controlled efficacy studies. The majority of patients were Caucasian (89.0%) and female (91.9%) with a mean age of 59 years (range, 18 to 98 years). Entry criteria required that patients have urge or mixed incontinence (with a predominance of urge) as evidenced by ≥ 6 urge incontinence episodes per week and ≥ 10 micturitions per day. Study 1 was a fixed-dose escalation design, whereas the other two studies used a dose-adjustment design in which each patient’s final dose was adjusted to a balance between improvement of incontinence symptoms and tolerability of side effects. All three studies included patients known to be responsive to oxybutynin or other anticholinergic medications, and these patients were maintained on a final dose for up to 2 weeks.

The efficacy results for the three controlled trials are presented in the following Tables 4, 5, and 6 and Figures 3, 4, and 5.

Table 4: Number of Urge Urinary Incontinence Episodes Per Week (Study 1)
Study 1 | n | Oxybutynin chloride extended-release tablets | n | Placebo
Mean Baseline | 34 | 15.9 | 16 | 20.9
Mean (SD) Change from Baseline† | 34 | -15.8 (8.9) | 16 | -7.6 (8.6)
95% Confidence Interval for Difference |  | (-13.6, -2.8) *
(Oxybutynin chloride extended- release tablets – Placebo)

*The difference between Oxybutynin chloride extended-release tablets and placebo was statistically significant.

†Covariate adjusted mean with missing observations set to baseline values

Figure 3: Mean Change (± SD) in Urge Urinary Incontinence Episodes Per Week from Baseline (Study 1)

The difference between Oxybutynin chloride extended-release tablets and placebo was statistically significant.

Table 5: Number of Urge Urinary Incontinence Episodes Per Week (Study 2)

Study 2 | n | Oxybutynin chloride extended-release tablets | n | oxybutynin
Mean Baseline | 53 | 27.6 | 52 | 23.0
Mean (SD) Change from Baseline† | 53 | -17.6 (11.9) | 52 | -19.4 (11.9)
95% Confidence Interval for Difference |  | (-2.8, 6.5)
(Oxybutynin chloride
extended-release
tablets – oxybutynin)

†Covariate adjusted mean with missing observations set to baseline values
Figure 4: Mean Change (±SD) in Urge Urinary Incontinence Episodes Per Week from Baseline (Study 2)

Table 6: Number of Urge Urinary Incontinence Episodes Per Week (Study 3)

Study 3 | n | Oxybutynin chloride extended-release tablets | n | oxybutynin
Mean Baseline | 111 | 18.9 | 115 | 19.5
Mean (SD) Change from Baseline† | 111 | -14.5 (8.7) | 115 | -13.8 (8.6)
95% Confidence Interval for Difference (Oxybutynin chloride extended-release tablets – oxybutynin) |  | (-3.0, 1.6) **

**The difference between Oxybutynin chloride extended-release tablets and oxybutynin fulfilled the criteria for comparable efficacy.

†Covariate adjusted mean with missing observations set to baseline values

Figure 5: Mean Change (±SD) in Urge Urinary Incontinence Episodes Per Week from

Baseline (Study 3)

*The difference between Oxybutynin chloride extended-release tablets and oxybutynin fulfilled the criteria for comparable efficacy.

16 HOW SUPPLIED/STORAGE AND HANDLING

Product: 50090-6840

NDC: 50090-6840-0 90 TABLET, EXTENDED RELEASE in a BOTTLE

NDC: 50090-6840-1 30 TABLET, EXTENDED RELEASE in a BOTTLE

17 PATIENT COUNSELING INFORMATION

- Patients should be informed that oxybutynin may produce angioedema that could result in life threatening airway obstruction. Patients should be advised to promptly discontinue oxybutynin therapy and seek immediate medical attention if they experience swelling of the tongue, edema of the laryngopharynx, or difficulty breathing.
- Patients should be informed that anticholinergic (antimuscarinic) agents such as oxybutynin chloride extended-release tablets, may produce clinically significant adverse reactions related to anticholinergic activity such as:
  - Urinary retention and constipation
  - Heat prostration due to decreased sweating. Heat prostration can occur when anticholinergic medicines are administered in the presence of high environmental temperature.
- Patients should be informed that anticholinergic medicines such as oxybutynin chloride extended-release tablets may produce drowsiness (somnolence), dizziness or blurred vision. Patients should be advised to exercise caution in decisions to engage in potentially dangerous activities until oxybutynin chloride extended-release tablets effects have been determined.
- Patients should be informed that alcohol may enhance the drowsiness caused by anticholinergic agents such as oxybutynin chloride extended-release tablets.
- Patients should be informed that oxybutynin chloride extended-release tablets should be swallowed whole with the aid of liquids. Patients should not chew, divide, or crush tablets. The medication is contained within a nonabsorbable shell designed to release the drug at a controlled rate. The tablet shell is eliminated from the body; patients should not be concerned if they occasionally notice in their stool something that looks like a tablet.
- Oxybutynin chloride extended-release tablets should be taken at approximately the same time each day.

For more information call Rising Pharma Holdings, Inc. at 1-844-874-7464.
Manufactured by:

Unique Pharmaceutical Laboratories
(A Div. of J. B. Chemicals & Pharmaceuticals Ltd.)
Mumbai, 400 030, India.

Distributed by:

Rising Pharma Holdings, Inc.

East Brunswick, NJ 08816

Revised: 05/2025

141691